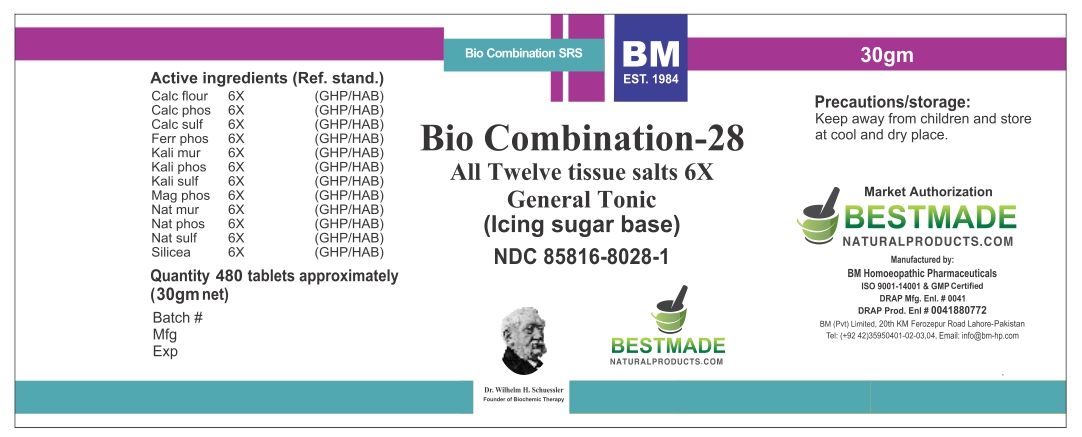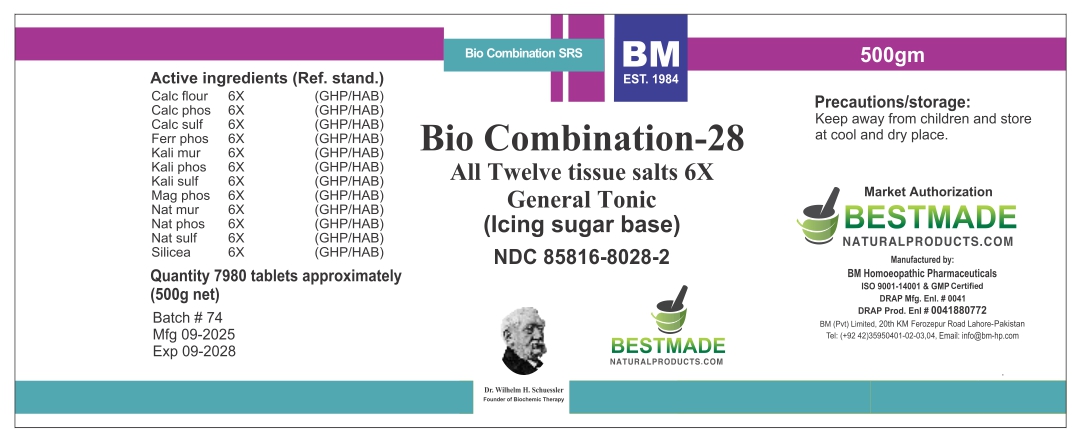 DRUG LABEL: BM BIO28 ICING SUGAR
NDC: 85816-8028 | Form: GLOBULE
Manufacturer: BM Private Limited
Category: homeopathic | Type: HUMAN OTC DRUG LABEL
Date: 20251202

ACTIVE INGREDIENTS: CALCIUM SULFATE ANHYDROUS 6 [hp_X]/1 g; MAGNESIUM PHOSPHATE, DIBASIC TRIHYDRATE 6 [hp_X]/1 g; POTASSIUM SULFATE 6 [hp_X]/1 g; CALCIUM FLUORIDE 6 [hp_X]/1 g; SODIUM PHOSPHATE, DIBASIC, HEPTAHYDRATE 6 [hp_X]/1 g; POTASSIUM PHOSPHATE, DIBASIC 6 [hp_X]/1 g; POTASSIUM CHLORIDE 6 [hp_X]/1 g; SODIUM SULFATE 6 [hp_X]/1 g; SODIUM CHLORIDE 6 [hp_X]/1 g; SILICON DIOXIDE 6 [hp_X]/1 g; TRIBASIC CALCIUM PHOSPHATE 6 [hp_X]/1 g; FERROSOFERRIC PHOSPHATE 6 [hp_X]/1 g
INACTIVE INGREDIENTS: SILICA DIMETHYL SILYLATE 0.001 g/1 g; MAGNESIUM STEARATE 0.01 g/1 g; POVIDONE K30 0.015 g/1 g; SUCROSE 0.973 g/1 g

BM BIO 28 ICING SUGAR

INACTIVE INGREDIENT

Sugar
PVP K 30
Magnesium Stearate
Aerosil

ACTIVE INGREDIENT

CALC SULPH, CALC FLUOR, CALC PHOS, FERR PHOS, KALI MUR, KALI PHOS, KALI SULPH, MAG PHOS, NAT PHOS, NAT SULPH, NAT MUR, SILICEA

INDICATIONS AND USAGE

check product leaflet

PURPOSE

check product leaflet

DOSAGE AND ADMINISTRATION

check product leaflet

Warnings:

Keep away from children and store at cool and dry place.

Warnings:

Keep away from children and store at cool and dry place.

PACKAGE LABEL

30g:

500g: